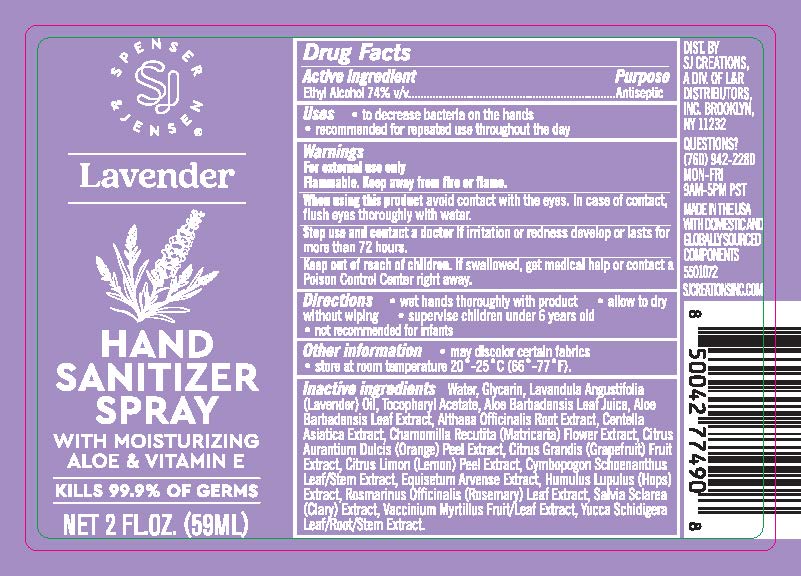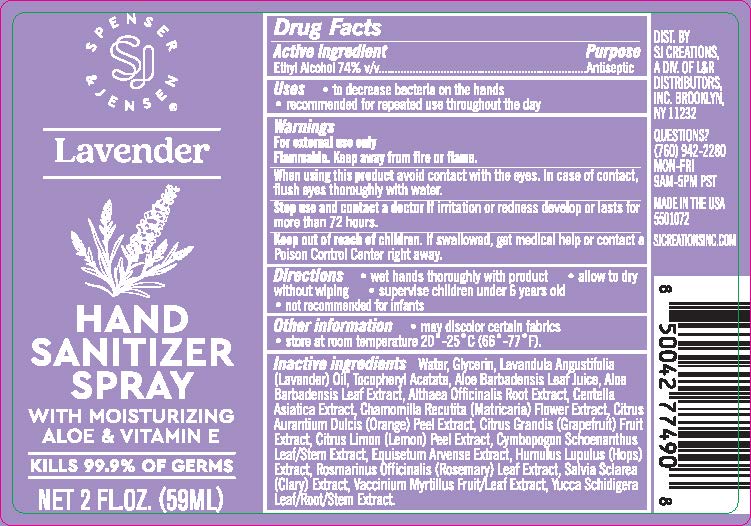 DRUG LABEL: Hand Sanitizer
NDC: 15127-009 | Form: SPRAY
Manufacturer: L&R Distributors, Inc.
Category: otc | Type: HUMAN OTC DRUG LABEL
Date: 20251201

ACTIVE INGREDIENTS: ALCOHOL 74 mL/100 mL
INACTIVE INGREDIENTS: GRAPEFRUIT PEEL; VACCINIUM MYRTILLUS WHOLE; HUMULUS LUPULUS WHOLE; ROSMARINUS OFFICINALIS WHOLE; .ALPHA.-TOCOPHEROL ACETATE; ALOE VERA LEAF; CHAMOMILE; ORANGE PEEL; WATER; GLYCERIN; CYMBOPOGON SCHOENANTHUS WHOLE; EQUISETUM ARVENSE WHOLE; SALVIA SCLAREA WHOLE; YUCCA SCHIDIGERA; LEMON PEEL; LAVENDER OIL; ALTHAEA OFFICINALIS ROOT; CENTELLA ASIATICA

ACTIVE INGREDIENT

Ethyl Alcohol 74% V/V

INDICATIONS AND USAGE

- For hand washing to decrease bacteria on the skin
- recommended for repeated use throughout the day

PUPOSE

ANTISEPTIC

WARNINGS

For external use only
Flammable. Keep away from fire or flame.
When using this product avoid contact with the eyes. In case of contact, flush eyes thoroughly with water.
Stop use and contact a doctor if irritation or redness develop or lasts for more than 72 hours.

KEEP OUT OF REACH OF CHILDREN

If swallowed, get medical help or contact a Poison Control Center right away.

DIRECTIONS

• wet hands thoroughly with product - • allow to dry without wiping - • supervise children under 6 years old - • not recommended for infants

OTHER INFORMATION

• may discolor certain fabrics - • store at room temperature 20°-25°C (66°-77°F).

INACTIVE INGREDIENTS

Water, Glycerin, Lavendula Angustifolia (Lavender) Oil, Tocopheryl Acetate, Aloe Barbadensis (Aloe Vera) Leaf Juice, Aloe Barbadensis Leaf Extract, Althaea Officinalis Root Extract, Centella Asiatica Extract, Chamomilla Recutita (Matricaria) Flower Extract, Citrus Aurantium Dulcis (Orange) Peel Extract, Citrus Grandis (Grapefruit) Fruit Extract, Citrus Limon (Lemon) Peel Extract, Cymbopogon Schoenanthus Leaf/Stem Extract, Equisetum Arvense Extract, Humulus Lupulus (Hops) Extract, Rosmarinus Officinalis (Rosemary) Leaf Extract, Salvia Sclarea (Clary) Extract, Vaccinium Myrtillus Fruit/Leaf Extract, Yucca Schidigera Leaf/Root/Stem Extract.

PRINCIPAL DISPLAY PANEL

NDC 15127-008-02